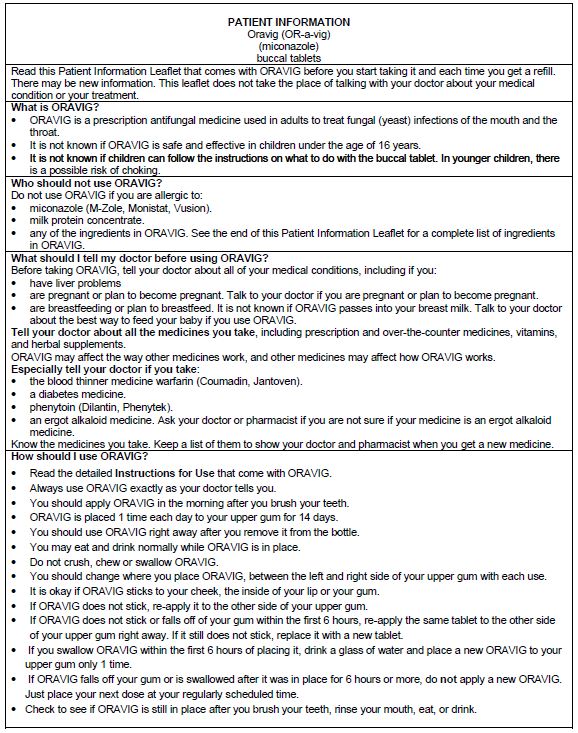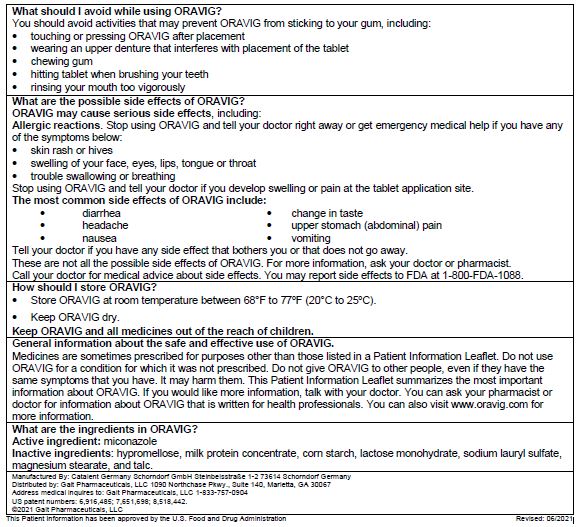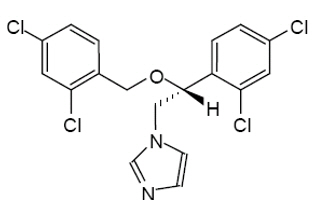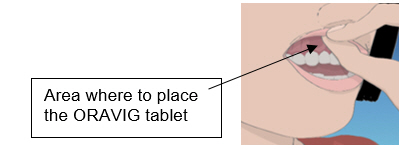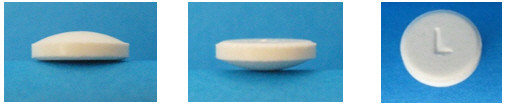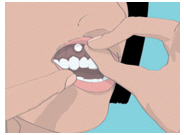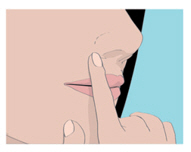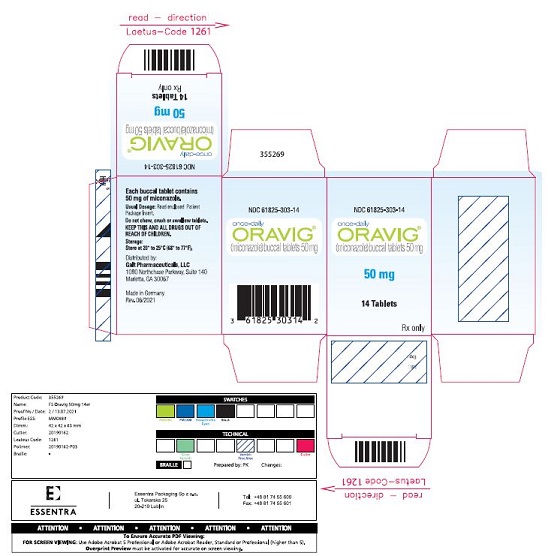 DRUG LABEL: Oravig
NDC: 61825-303 | Form: TABLET
Manufacturer: Galt Pharmaceuticals, LLC
Category: prescription | Type: HUMAN PRESCRIPTION DRUG LABEL
Date: 20260108

ACTIVE INGREDIENTS: MICONAZOLE 50 mg/1 1
INACTIVE INGREDIENTS: HYPROMELLOSE, UNSPECIFIED; STARCH, CORN; LACTOSE MONOHYDRATE; SODIUM LAURYL SULFATE; MAGNESIUM STEARATE; TALC; CASEIN

HIGHLIGHTS OF PRESCRIBING INFORMATION These highlights do not include all the information needed to use ORAVIG safely and effectively. See full prescribing information for ORAVIG.
ORAVIG (miconazole) buccal tablets Initial U.S. Approval: January 1974

1 INDICATIONS & USAGE

ORAVIG is an azole antifungal indicated for the local treatment of oropharyngeal candidiasis in adults.

2 DOSAGE & ADMINISTRATION

- Application of one ORAVIG 50 mg buccal tablet to the gum region once daily for 14 consecutive days (2.1).
- Instruct patients not to crush, chew, or swallow tablets (2.2).

3 DOSAGE FORMS & STRENGTHS

50 mg buccal tablets

4 CONTRAINDICATIONS

Known hypersensitivity to miconazole, milk protein concentrate, or any other component of the product.

5 WARNINGS AND PRECAUTIONS

Hypersensitivity reactions: Anaphylactic reactions have been reported in patients receiving miconazole. Discontinue ORAVIG immediately at the first sign of hypersensitivity (5.1).

6 ADVERSE REACTIONS

Most common adverse reactions (≥2%) are: diarrhea, headache, nausea, dysgeusia, upper abdominal pain, and vomiting (6.1).
To report SUSPECTED ADVERSE REACTIONS, contact Galt Pharmaceuticals, LLC Marietta, GA 30067 at 1-833-757-0904 or FDA at 1-800-FDA-1088 or www.fda.gov/medwatch.

7 DRUG INTERACTIONS

Warfarin: Miconazole may enhance anticoagulant effect. Monitor prothrombin time, INR, and watch for bleeding (7.1).

8 USE IN SPECIFIC POPULATIONS

- Pregnancy: Based on animal data, may cause fetal harm (8.1).
- Pediatric Use: Safety and efficacy not established in patients less than 16 years of age (8.4).

See 12 for PATIENT COUNSELING INFORMATION and FDA-Approved Patient Labeling

FULL PRESCRIBING INFORMATION

1 INDICATIONS & USAGE

ORAVIG is indicated for the local treatment of oropharyngeal candidiasis (OPC) in adults.

2 DOSAGE & ADMINISTRATION

2.1 Basic Dosing Information

The recommended dosing schedule for ORAVIG is the application of one 50 mg buccal tablet to the upper gum region (canine fossa) once daily for 14 consecutive days.

2.2 Administration Instructions

ORAVIG should be applied in the morning, after brushing the teeth. The tablet should be applied with dry hands. The rounded side surface of the tablet should be placed against the upper gum just above the incisor tooth (canine fossa) and held in place with slight pressure over the upper lip for 30 seconds to ensure adhesion. The tablet is round on one side for comfort, but either side of the tablet can be applied to the gum.

Once applied, ORAVIG stays in position and gradually dissolves. [ See Clinical Pharmacology (12.3)] Subsequent applications of ORAVIG should be made to alternate sides of the mouth. Before applying the next tablet, the patient should clear away any remaining tablet material. In addition,

- ORAVIG should not be crushed, chewed or swallowed.
- Food and drink can be taken normally when ORAVIG is in place but chewing gum should be avoided.
- If ORAVIG does not adhere or falls off within the first 6 hours, the same tablet should be repositioned immediately. If the tablet still does not adhere, a new tablet should be placed.
- If ORAVIG is swallowed within the first 6 hours, the patient should drink a glass of water and a new tablet should be applied only once.
- If ORAVIG falls off or is swallowed after it was in place for 6 hours or more, a new tablet should not be applied until the next regularly scheduled dose. [ see Patient Counseling Information (17)].

3 DOSAGE FORMS & STRENGTHS

ORAVIG is a buccal tablet containing 50 mg of miconazole. ORAVIG tablets are round, off-white tablets, with a rounded side and a flat side. The tablets are marked with an “L” on the flat side.

4 CONTRAINDICATIONS

ORAVIG is contraindicated in patients with known hypersensitivity (e.g., anaphylaxis) to miconazole, milk protein concentrate, or any other component of the product.

5 WARNINGS AND PRECAUTIONS

5.1 Hypersensitivity

Allergic reactions, including anaphylactic reactions and hypersensitivity, have been reported with the administration of miconazole products, including ORAVIG. Discontinue ORAVIG immediately at the first sign of hypersensitivity.

There is no information regarding cross-hypersensitivity between miconazole and other azole antifungal agents. Monitor patients with a history of hypersensitivity to azoles.

6 ADVERSE REACTIONS

The following serious adverse drug reactions are discussed in detail in other sections of labeling:

- Hypersensitivity reactions [see Warnings and Precautions (5.1)]

6.1 Clinical Trial Experience

Because clinical trials are conducted under widely varying conditions, adverse reaction rates observed in the clinical trials of a drug cannot be directly compared to rates in the clinical trials of another drug and may not reflect the rates observed in clinical practice.

The overall safety of ORAVIG was assessed in 480 adult subjects: 315 HIV-infected subjects, 147 subjects with head and neck cancer, and 18 healthy subjects.

HIV Infected Patients
Two trials were conducted in immunocompromised HIV-infected patients: one randomized, double-blind, double-dummy, active-controlled design (N = 290 ORAVIG, 287 control) and one non-comparative trial (N = 25).

In the randomized, double blind trial (Study 1), 290 HIV infected subjects used ORAVIG once daily for 14 days, and 287 subjects used 10 mg clotrimazole troches five times daily for 14 days. Adverse reactions occurring in ≥ 2% of patients in either treatment are presented in Table 1.

Table 1 Adverse Reactions (Treatment-Emergent) Occurring in ≥ 2% of HIV-Infected Patients in the Controlled Clinical Trial

Adverse Reaction (MedDRA v 9.1 System Organ Class and Preferred Term) | ORAVIG N = 290 (%) | Clotrimazole troches N = 287 (%)
Patients with any adverse reaction during the study | 158 (54.5) | 146 (50.9)
Gastrointestinal disorders Diarrhea Nausea Vomiting Dry mouth Abdominal pain upper | 25.9 9.0 6.6 3.8 2.8 1.7 | 23.7 8.0 7.7 3.1 1.7 2.8
Infections and infestations Upper respiratory infection Gastroenteritis | 15.9 2.1 1.4 | 17.1 2.4 2.8
Nervous system disorders Headache Ageusia | 13.1 7.6 2.4 | 8.4 6.6 0.3
Blood and lymphatic disorders Anemia Lymphopenia Neutropenia | 6.9 2.8 1.7 0.7 | 8.4 1.7 2.1 2.1
General disorders and administration site conditions Fatigue Pain | 6.6 2.8 1.0 | 8.0 2.1 2.8
Respiratory/thoracic Cough Pharyngeal pain | 5.2 2.8 0.7 | 7.7 1.7 2.4
Investigations Increased GGT | 5.5 1.0 | 6.3 2.8

Overall local adverse reactions, including oral discomfort, oral burning, oral pain, gingival pain, gingival swelling, gingival pruritis, tongue ulceration, mouth ulceration, glossodynia, dry mouth, application site pain or discomfort, toothache, loss of taste, and altered taste, were reported by 35 (12.1%) patients who received miconazole buccal tablet compared to 27 (9.4%) patients who received clotrimazole troches.

Head and Neck Cancer Patients
In the randomized, open-label comparative trial of oropharyngeal candidiasis in patients with head and neck cancer who had received radiation therapy (Study 2), 147 patients used ORAVIG once daily for 14 days and 147 patients used 125 mg of miconazole oral gel four times daily for 14 days. Adverse reactions occurring in ≥2% of patients in either arm are listed in Table 2.

Table 2: Adverse Reactions (Treatment-Emergent) Occurring in ≥ 2% of Patients with Head and Neck Cancer who had Received Radiation Therapy (Controlled Clinical Trial)

Adverse Reaction (MedDRA v 9.1 System Organ Class and Preferred Term) | ORAVIG N = 147 (%) | Miconazole gel N = 147 (%)
Patients with at least one adverse reaction | 30 (20.4) | 32 (21.8)
Gastrointestinal disorders Abdominal pain, upper Oral discomfort Nausea Vomiting Glossodynia | 8.8 1.4 2.7 0.7 0.7 0 | 13.6 2.0 2.7 2.7 2.0 2.0
Nervous system disorders Dysgeusia | 5.4 4.1 | 1.4 0
Skin and subcutaneous Pruritus | 3.4 2.0 | 0.7 0.7

Overall local adverse reactions, including oral discomfort, oral pain, dry mouth, glossodynia, loss of taste, altered taste, tongue ulceration, mouth ulceration, tooth disorder, and application site discomfort or pain, were experienced by 14 (9.5%) patients who used ORAVIG compared to 16 (10.9%) patients who used miconazole gel.

Overall ORAVIG Safety Experience In Patients and Healthy Subjects
Adverse reactions reported in the overall safety database of 480 subjects who received miconazole buccal tablet is listed in Table 3.

Table 3 Adverse Reactions Reported in ≥ 2% of Patients and Healthy Subjects who Received ORAVIG in Clinical Trials

Adverse reaction (MedDRA v 9.1 System Organ Class and Preferred Term) | ORAVIG N = 480 (%)
Patients with at least one AE | 209 (43.5)
Gastrointestinal disorders Diarrhea Nausea Abdominal pain upper Vomiting | 20.6 6.0 4.6 2.5 2.5
Infections and infestations | 11.9
Nervous system disorders Headache Dysgeusia | 10.6 5.0 2.9

Discontinuation of ORAVIG due to adverse drug reactions occurred in 0.6% overall.

7 DRUG INTERACTIONS

7.1 Warfarin

Concomitant administration of miconazole and warfarin has resulted in enhancement of anticoagulant effect. Cases of bleeding and bruising following the concomitant use of warfarin and topical, intravaginal, or oral miconazole were reported. Closely monitor prothrombin time, International Normalized Ratio (INR), or other suitable anticoagulation tests if ORAVIG is administered concomitantly with warfarin. Also monitor for evidence of bleeding.

7.2 Drugs Metabolized Through CYP 2C9 and 3A4

No formal drug interaction studies have been performed with ORAVIG. Miconazole is a known inhibitor of CYP2C9 and CYP3A4. Although the systemic absorption of miconazole following ORAVIG administration is minimal and plasma concentrations of miconazole are substantially lower than when given intravenously, the potential for interaction with drugs metabolized through CYP2C9 and CYP3A4 such as oral hypoglycemics, phenytoin, or ergot alkaloids cannot be ruled out.

8 USE IN SPECIFIC POPULATIONS

8.1 Pregnancy

Risk Summary

Based on findings from animal data, ORAVIG may cause fetal harm when administered to pregnant women. There are no available data on ORAVIG use in pregnant women to evaluate for a drug-associated risk of major birth defects, miscarriage or adverse maternal or fetal outcomes. In animal reproduction studies, prolonged gestation, dystocia and/or increased number of resorptions were observed after oral administration of miconazole nitrate during organogenesis to pregnant rats and rabbits. (See Data). Advise pregnant women of the potential risk to a fetus.

The background risk of major birth defects and miscarriage for the indicated population is unknown. All pregnancies have a background risk of birth defect, loss, or other adverse outcomes. In the US general population, the estimated background risk of major birth defects and miscarriages in clinically recognized pregnancies is 2% to 4% and 15% to 20%, respectively.

Data

Animal Data:

Miconazole nitrate administered orally at doses of 80 mg/kg/day or higher to pregnant rats or rabbits crossed the placenta and resulted in embryo- and fetotoxicity, including increased fetal resorptions. These doses also resulted in prolonged gestation and dystocia in rats, but not in rabbits. Embryofetotoxicity was not observed in intravenous studies with miconazole at lower doses of 40 mg/kg/day in rats and 20 mg/kg/day in rabbits, which are approximately 8 times higher than the dose a patient would receive if she swallowed an ORAVIG buccal tablet, based on body surface area comparisons. Teratogenicity was not reported in any animal study with miconazole.

8.2 Lactation

Risk Summary

There is no available information on the presence of miconazole in human milk, or the effects on the breastfed child, or the effects on milk production following use of ORAVIG.

The developmental and health benefits of breastfeeding should be considered along with the mother’s clinical need for ORAVIG and any potential adverse effects on the breastfed infant from ORAVIG or from the underlying maternal condition.

8.4 Pediatric Use

Safety and effectiveness of ORAVIG in pediatric patients below the age of 16 years have not been established. The ability of pediatric patients to comply with the application instructions has not been evaluated. Use in younger children is not recommended due to potential risk of choking.

8.5 Geriatric Use

Clinical studies of ORAVIG did not include sufficient numbers of subjects aged 65 and over to determine whether they respond differently from younger subjects.

8.6 Hepatic Impairment

Miconazole is metabolized by the liver. While miconazole systemic exposure is minimal following the application of ORAVIG, ORAVIG should be administered with caution in patients with hepatic impairment.

8.7 Renal Impairment

Less than 1% of miconazole is excreted as unchanged drug in the urine; therefore, no adjustment to therapy is necessary in patients with renal impairment.

10 OVERDOSAGE

Overdose with miconazole in humans has not been reported in the literature.

Miconazole absorption and systemic exposure following application of ORAVIG are minimal [see Clinical Pharmacology (12.3)].

Symptomatic and supportive care is the basis for management.

11 DESCRIPTION

ORAVIG (miconazole) buccal tablets are applied topically to the gum once daily and release miconazole as the buccal tablet gradually dissolves [see Clinical Pharmacology (12.3)].

Miconazole is an imidazole antifungal agent and is described chemically as 1-[(2RS)-2-[(2,4-dichlorobenzyl)oxy]-2-(2,4-dichlorophenyl)ethyl]-1H-imidazole with an empirical formula of C18H14Cl4N2O and a molecular weight of 416.13. The structural formula is shown in Figure 1.
Figure 1: Structural Formula of Miconazole
Miconazole drug substance is a white to almost white powder.

ORAVIG contains 50 mg of miconazole base, USP and the following inactive ingredients: hypromellose, USP; milk protein concentrate; corn starch, NF; lactose monohydrate, NF; sodium lauryl sulfate, NF; magnesium stearate, NF; and talc, USP.

12 CLINICAL PHARMACOLOGY

12.1 Mechanism of Action

Miconazole is an antifungal drug [see Microbiology (12.4)].

12.3 Pharmacokinetics

Absorption and Distribution

Salivary

Single dose application of ORAVIG containing 50 mg of miconazole to the buccal mucosa of 18 healthy volunteers provided mean maximum salivary concentrations of 15 mcg/mL at 7 hours after application of the tablet. This provided an average saliva exposure to miconazole estimated from the AUC (0-24h) of 55.23 mcg·h/mL. The pharmacokinetic parameters of miconazole in the saliva of healthy volunteers are provided in Table 4.

Table 4: Pharmacokinetic (PK) Parameters of Miconazole in Saliva Following Application of a Single ORAVIG 50 mg Tablet in Healthy Volunteers (N = 18)

Salivary PK Parameters (N = 18) | Mean ±SD (Min - Max)
AUC0-24h (mcg-h/mL) | 55.2 ±35.1 (0.5 – 128.3)
Cmax (mcg/mL) | 15.1 ±16.2 (0.5 – 64.8)
Tmax (hour) | 7* (2.0 – 24.1)

*Median

In healthy volunteers, the duration of buccal adhesion was on average 15 hours following a single dose application of ORAVIG 50 mg.

Plasma

Plasma concentrations of miconazole were below the lower limit of quantification (0.4 mcg/mL) in 157/162 (97%) samples from healthy volunteers following single-dose application of ORAVIG 50 mg. Measurable plasma concentrations ranged from 0.5 to 0.83 mcg/mL.

Plasma concentrations of miconazole evaluated after 7 days of treatment in 40 HIV-positive patients were all below the limit of quantification (0.1 mcg/mL).

Metabolism and Excretion

Most of the absorbed miconazole is metabolized by the liver with less than 1% of the administered dose found unchanged in urine. In healthy volunteers, the terminal half-life is 24 hours following systemic administration. There are no active metabolites of miconazole.

Food Effect

There was no formal food effect study conducted with ORAVIG; however, in clinical studies patients were allowed to eat and drink while taking ORAVIG.

12.4 Microbiology

Mechanism of Action

Miconazole inhibits the enzyme cytochrome P450 14α-demethylase which leads to inhibition of ergosterol synthesis, an essential component of the fungal cell membrane. Miconazole also affects the synthesis of triglycerides and fatty acids and inhibits oxidative and peroxidative enzymes, increasing the amount of reactive oxygen species within the cell.

Antimicrobial Activity

Miconazole is active against Candidaalbicans, C. parapsilosis and C. tropicalis. Correlation between minimum inhibitory concentration (MIC) results in vitro and clinical outcome has yet to be established.

Resistance

In vitro studies have shown that some Candida strains that demonstrate reduced susceptibility to one antifungal azole may also exhibit reduced susceptibility to other azoles suggesting cross-resistance.

Clinically relevant resistance to systemically utilized triazoles may occur in Candida species. Resistance may occur by multiple mechanisms such as changes in amino acids and/or in the regulation of the target enzyme and of a variety of efflux pump proteins. Multiple mechanisms may co‑exist in the same isolate. Resistance breakpoints, correlating in vitro activity with clinical efficacy, have not been established for miconazole.

13 NONCLINICAL TOXICOLOGY

13.1 Carcinogenesis & Mutagenesis & Impairment Of Fertility

Carcinogenicity studies with miconazole have not been conducted.
Miconazole nitrate was not genotoxic when tested in vitro in a bacterial reverse mutation (Ames) assay or in an in vivo mouse bone marrow micronucleus test. Intraperitoneal injections of miconazole to mice induced chromosomal aberrations in spermatocytes and bone marrow cells, and morphologic abnormalities in sperm at doses similar to or below clinical doses. However, no impairment of fertility was observed in intravenous studies with miconazole at 40 mg/kg/day in rats or 20 mg/kg/day in rabbits, which are approximately 8 times higher than the dose a patient would receive if she swallowed an ORAVIG buccal tablet, based on body surface area comparisons.

13.2 Animal Pharmacology & OR Toxicology

Local tolerance studies (LLNA sensitization test and tolerance study on the jugal mucosa of hamster) did not reveal any toxicity.

14 CLINICAL STUDIES

Study in HIV Infected Patients

The efficacy and safety of ORAVIG in the treatment of OPC was evaluated in a randomized, double-blind, double-dummy, multicenter trial comparing ORAVIG 50 mg once daily for 14 consecutive days (n = 290) with clotrimazole troches 10 mg 5 times per day for 14 days (n = 287) in HIV-positive patients with OPC. Seventy-five percent of patients were not receiving highly active antiretroviral treatment, 5% had CD4+ cell count < 50 cells/mm^3, and 17% had a history of previous OPC. The mean viral load was 117,000 copies/mL. Patients were required to have symptoms and microbiological documentation of OPC for study entry. Most of the infections were caused by C. albicans (85%), followed by C. tropicalis (9%), and C. parapsilosis (3%). About 2% of the subjects were infected with more than one Candida species.

Clinical cure [defined as a complete resolution of both signs and symptoms of OPC at the test of cure (TOC) visit (days 17-22)], and clinical relapse by days 35-38 (21-24 days after end of therapy) are presented in Table 5. Mycological cure [defined as eradication (i.e., no yeast isolates) of Candida species] at the TOC visit (days 17-22) is also reported in the table.

Table 5: Clinical Cure and Mycological Cure at the TOC Visit and Relapse at Days 35-38 in HIV Infected Patients

 | ORAVIG 50 mg N=290a (%) | Clotrimazole troches N=287a (%)
Clinical cure† | 176 (60.7%) | 187 (65.2%)
Clinical relapse‡
Yesb | 48 (27.3%) | 52 (27.8%)
No | 124 (70.5%) | 133 (71.1%)
Missing | 4 (2.3%) | 2 (1.1%)
Mycological cure | 79 (27.2%) | 71 (24.7%)

a Analysis population includes all randomized patients who took at least 1 dose of study medication. One randomized subject excluded from the ORAVIG arm.

b In those subjects who relapsed, the mean time to relapse was 15.3 days (SD 4.6) and 15.7 days (SD 6.6), in the ORAVIG and Clotrimazole treatment arms, respectively.

† Difference in clinical cure rates (ORAVIG-clotrimazole troche) was -4.5%, with a 95% CI: (-12.4%, 3.4%).

‡ Percentage based on those who had clinical cure.

Study in Head and Neck Cancer Patients

The efficacy and safety of ORAVIG 50 mg was evaluated in an open-label, randomized, multicenter trial comparing ORAVIG 50 mg once daily for 14 days to miconazole oral gel 125 mg four times daily for 14 days in head and neck cancer patients who had received radiation therapy. Most of the infections were caused by C. albicans (71%), and C. tropicalis (8%). About 7% of the subjects were infected with more than one Candida species. Success rates of treatment at day 14 [defined as a complete (complete disappearance of candidiasis lesions) or partial response (improvement by at least 2 points of the score for extent of oral lesion compared with the score at day 1) based on a blind assessment] are shown in Table 6. Also reported in Table 6 are relapse rate at day 30, and mycologic cure assessed at day 14.

Table 6: Clinical Success and Mycological Cure at Day 14, in Patients with Head and Neck Cancer who had Received Radiation Therapy

 | ORAVIG 50 mg N=148a (%) | Miconazole oral gel N=146a (%)
Success rate (CR+PR) b | 79 (53.4%) | 69 (46.6%)
CR† | 74 (50.0%) | 64 (43.8%)
Clinical relapse‡
Yes c | 14 (18.9%) | 8 (12.5%)
No | 59 (79.7%) | 56 (87.5%)
Missing | 1 (1.4%) | 0
Mycological cure | 66 (44.6%) | 78 (53.4%)

a Analysis population includes all subjects who received at least one dose of study medication. Reasons for not receiving treatment included negative mycological culture, informed consent withdrawn, or lost during screening. Six patients excluded per arm.

bCR: complete response; PR: partial response

cIn those subjects who relapsed, the mean time to relapse was 18.8 days (SD 16.3) and 20.6 days (SD 13.5), in the ORAVIG and Miconazole oral gel group, respectively.

†Difference in clinical complete response rates (ORAVIG-Miconazole oral gel) was 6.2%, with a 95% CI: (-5.2%, 17.6%).

‡Percentage based on those who had complete response.

16 HOW SUPPLIED/STORAGE AND HANDLING

ORAVIG 50 mg buccal tablets are supplied as off-white tablets containing 50 mg of miconazole. ORAVIG tablets have a rounded side and a flat side. ORAVIG tablets are packaged in bottles of 14 tablets (NDC 61825-303-14).

ORAVIG should be stored at 20 to 25oC (68 to 77oF) [see USP controlled room temperature]; excursions between 15 and 30oC permitted at room temperature. Protect from moisture, and keep out of reach of children.

17 PATIENT COUNSELING INFORMATION

Advise the patient to read the FDA-approved patient labeling (Patient Information and Instructions for Use).
Important Administration Instructions
The tablet should be used immediately after removal from the bottle.
• Instruct patients not to crush, chew, or swallow the tablet.
• The rounded side of the tablet should be applied to the upper gum above the incisor tooth in the morning, after brushing the teeth.
• The tablet should be held in place for 30 seconds with a slight pressure of the finger over the upper lip to make the tablet stick to the gum.
• The tablet may be used if it sticks to the cheek, inside of the lip or the gum.
• If the tablet does not adhere, it should be repositioned.
• As the ORAVIG tablet absorbs moisture from the mouth, it will slowly dissolve over time and should be left in place – there is no need to remove the tablet.
• Subsequent applications of ORAVIG should be made to alternate sides of the gum.
• If ORAVIG does not stick or falls off within the first 6 hours, the same tablet should be repositioned immediately. If the tablet does not adhere, a new tablet should be placed.
• If ORAVIG is swallowed within the first 6 hours, the patient should drink a glass of water and a new tablet should be applied only once.
• If ORAVIG falls off or is swallowed after it was in place for 6 hours or more, a new tablet should not be applied until the next regularly scheduled dose.
Patients should avoid situations that could interfere with the sticking of the tablet including:
• touching or pressing the tablet after placement
• wearing upper denture
• chewing gum
• hitting tablet when brushing teeth
• rinsing mouth too vigorously
Hypersensitivity and Other Adverse Reactions
Patients who develop hives, skin rash, or other symptoms of an allergic reaction, and patients who develop swelling or pain, at the tablet application site should stop ORAVIG and contact a healthcare provider. Patients may experience other adverse reactions including diarrhea, headache, nausea, and change in taste.
Potential Embryo-fetal Toxicity
Advise pregnant women and females of reproductive potential of the potential risk to a fetus. Advise females to inform their healthcare provider of a known or suspected pregnancy [see Use in Specific Populations (8.1)].
Manufactured By:
Catalent Germany Schorndorf GmbH
Steinbeisstraße 1-2
73614 Schorndorf
Germany
Distributed by:
Galt Pharmaceuticals, LLC
1090 Northchase Pkwy., Suite 140
Marietta, GA 30067
Address medical inquires to:
Galt Pharmaceuticals, LLC
1-833-757-0904
US patent numbers: 6,916,485; 7,651,698; 8,518,442.
©2021 Galt Pharmaceuticals, LLC

INSTRUCTIONS FOR USE
Oravig (OR-a-vig)
(miconazole)
buccal tablets
Read this Instructions for Use before you start using ORAVIG and each time you get a refill. There may be new information. This information does not take the place of talking to your doctor about your medical condition or treatment. Talk to your doctor or pharmacist if you have any questions about how to use ORAVIG.
How should I store ORAVIG?
• Store ORAVIG at room temperature between 68°F to 77oF (20°C to 25oC).
• Keep ORAVIG dry.
Keep ORAVIG and all medicines out of the reach of children.
How to use ORAVIG?
Before applying the ORAVIG tablet
Step 1. Locate the area on the upper gum, just above the left or the right incisor tooth. The incisor tooth is the tooth just to the right or left of your two front teeth (See Figure A).

Step 2. With dry hands, take 1 ORAVIG tablet out of the bottle. ORAVIG is round on one side and flat on the other side (See Figure B). The tablet is marked with an “L” on the flat side.

Applying the ORAVIG tablet
Step 3. Place the flat side of the ORAVIG tablet on your dry fingertip. Gently push the round side of the tablet against your upper gum in the area shown in Figure C. Push the ORAVIG tablet up as high as it will go on your gum. The flat side will be facing the inside of your lip.

Step 4. Hold the ORAVIG tablet in place by applying a slight pressure with your finger on the outside of your upper lip for 30 seconds (See Figure D). This will make the tablet stick to your gum.

Step 5. Leave the ORAVIG tablet in place until it dissolves. Do not remove the tablet.
Step 6. Before applying your next dose, be sure to clear away any remaining ORAVIG tablet material on
your gum.
Manufactured By: Catalent Germany Schorndorf GmbH Steinbeisstraße 1-2 73614 Schorndorf Germany
Distributed by: Galt Pharmaceuticals, LLC 1090 Northchase Pkwy., Suite 140, Marietta, GA 30067
Address medical inquires to: Galt Pharmaceuticals, LLC 1-833-757-0904
US patent numbers: 6,916,485; 7,651,698; 8,518,442.
©2021 Galt Pharmaceuticals, LLC
This Instructions for Use has been approved by the U.S. Food and Drug Administration
Approved: 06/2021

PACKAGE LABEL.PRINCIPAL DISPLAY PANEL

NDC 61825-303-14
once-daily
ORAVIG®
(miconazole) buccal tablets 50 mg
50 mg
14 Tablets
Rx only